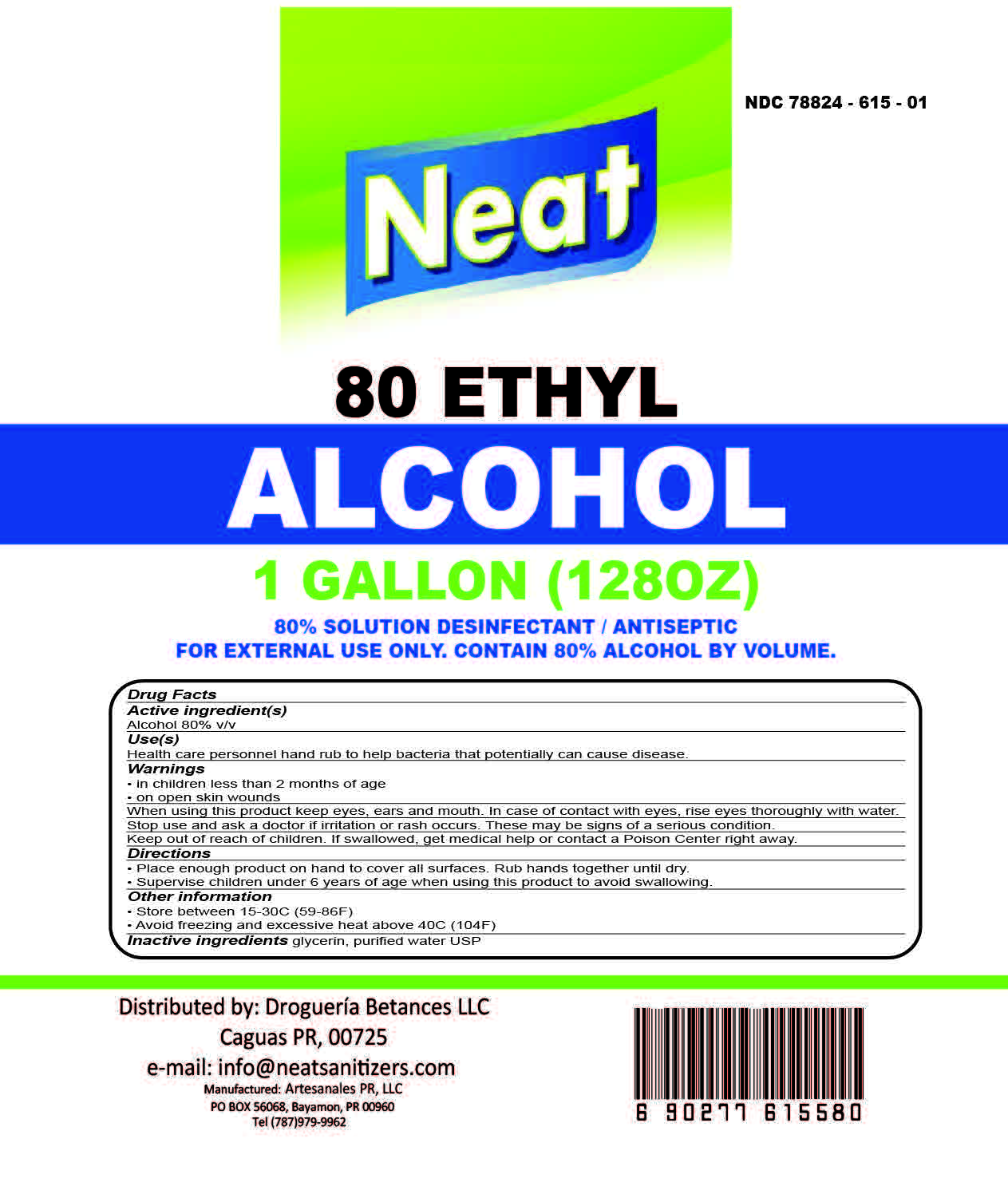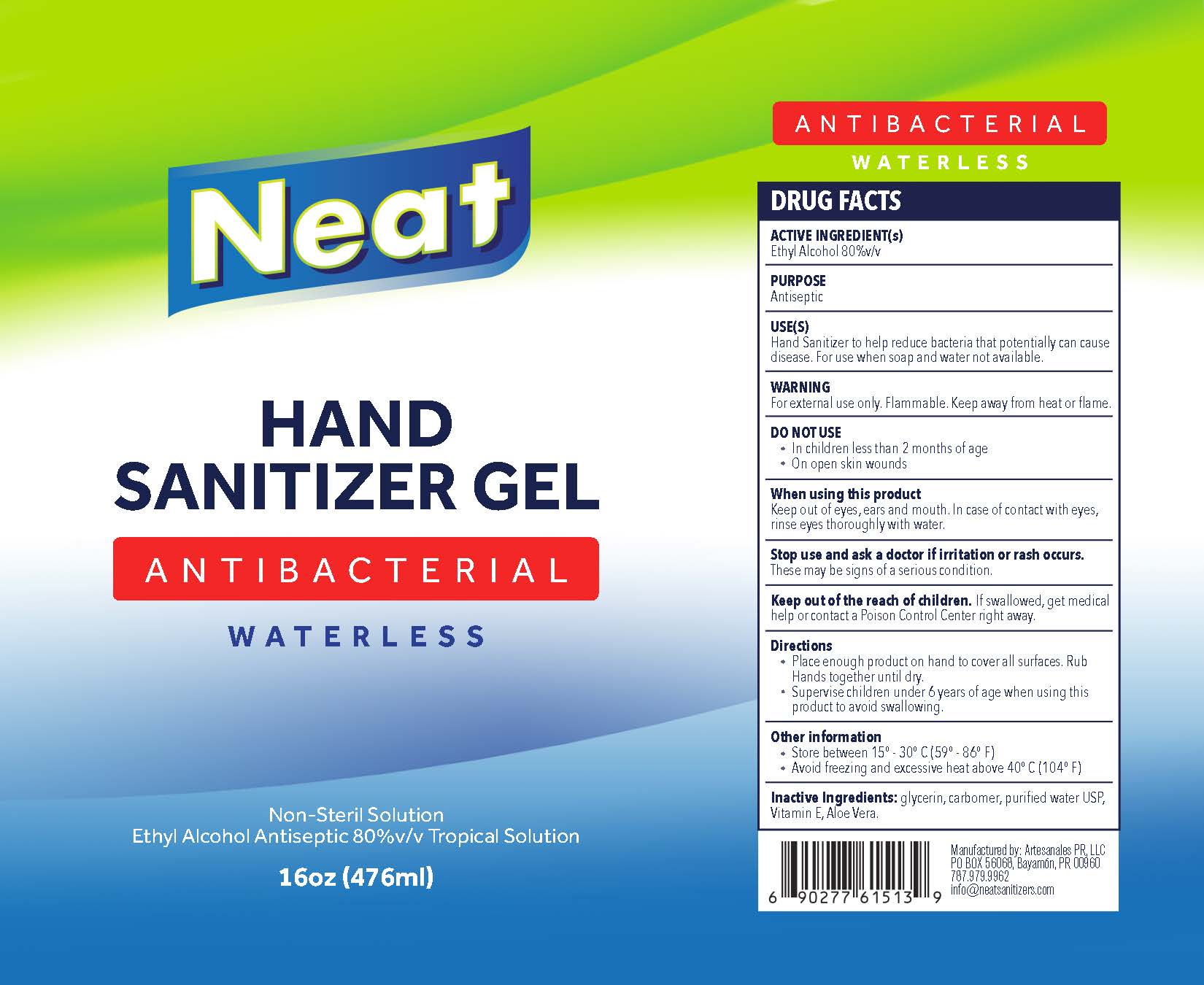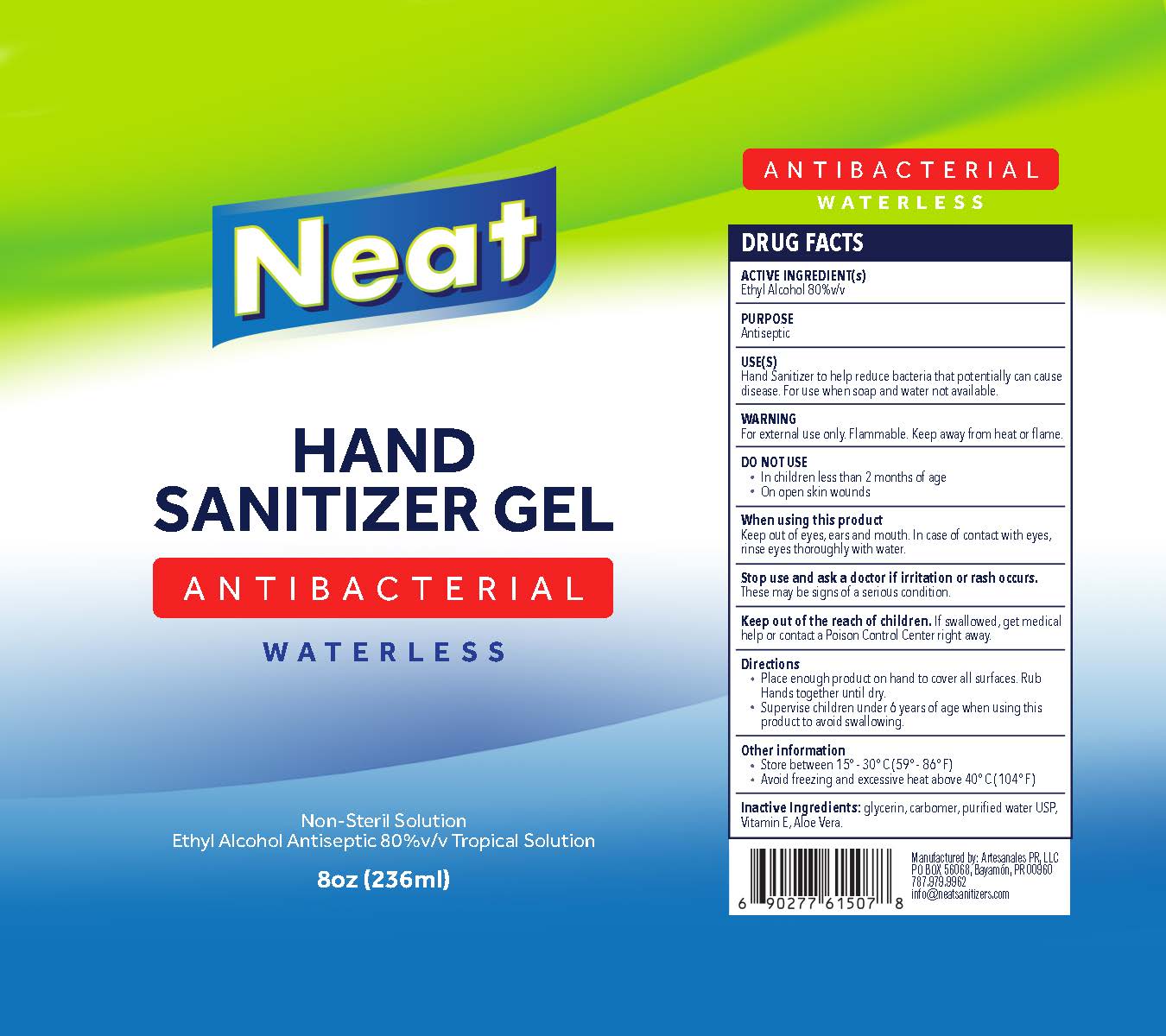 DRUG LABEL: Neat Hand Sanitizer
NDC: 78824-615 | Form: LIQUID
Manufacturer: Artesanales P.R. LLC
Category: otc | Type: HUMAN OTC DRUG LABEL
Date: 20240425

ACTIVE INGREDIENTS: ALCOHOL 80 mL/100 mL
INACTIVE INGREDIENTS: WATER

Hand Sanitizer Neat 80% Ethyl

.

The hand sanitizer is manufactured using only the following United States Pharmacopoeia (USP) grade ingredients in the preparation of the product (percentage in final product formulation)

The firm does not add other active or inactive ingredients. Different or additional ingredients may impact the quality and potency of the product.

Active Ingredient(s)

Alcohol 80% v/v. Purpose: Antiseptic

Purpose

Antiseptic, Hand Sanitizer

Use

Hand Sanitizer to help reduce bacteria that potentially can cause disease. For use when soap and water are not available.

Warnings

For external use only. Flammable. Keep away from heat or flame

Do not use

- in children less than 2 months of age
- on open skin wounds

When using this product keep out of eyes, ears, and mouth. In case of contact with eyes, rinse eyes thoroughly with water.
Stop use and ask a doctor if irritation or rash occurs. These may be signs of a serious condition.
Keep out of reach of children. If swallowed, get medical help or contact a Poison Control Center right away.

Stop use and ask a doctor if irritation or rash occurs. These may be signs of a serious condition.

Keep out of reach of children. If swallowed, get medical help or contact a Poison Control Center right away.

Directions

- Place enough product on hands to cover all surfaces. Rub hands together until dry.
- Supervise children under 6 years of age when using this product to avoid swallowing.

Other information

- Store between 15-30C (59-86F)
- Avoid freezing and excessive heat above 40C (104F)

Inactive ingredients

glycerin, hydrogen peroxide, purified water USP